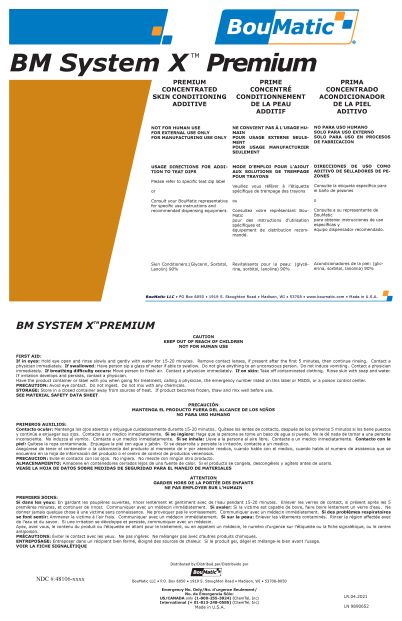 DRUG LABEL: BouMatic Syst X Premium
NDC: 48106-2037 | Form: LIQUID
Manufacturer: BOUMATIC, LLC
Category: animal | Type: OTC ANIMAL DRUG LABEL
Date: 20210430

ACTIVE INGREDIENTS: GLYCERIN 50 g/100 g
INACTIVE INGREDIENTS: SORBITOL SOLUTION 70% 20 g/100 g; PEG-75 LANOLIN 20 g/100 g; water 10 g/100 g

BouMatic Syst X Premium

Precautions & Hazards

NOT FOR HUMAN USE
FOR EXTERNAL USE ONLY
FOR MANUFACTURING USE ONLY

General Storage

Store in a closed container away from sources of heat. If product becomes frozen, thaw and mix well before use.

Use Directions

Consult your BouMatic representative
for specific use instructions and
recommended dispensing equipment.

BouMatic Syst X Premium